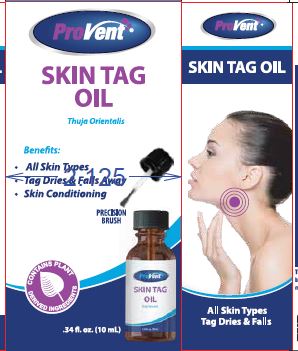 DRUG LABEL: Skin Tag Relief
NDC: 68229-100 | Form: OIL
Manufacturer: Quest Products, Inc.
Category: homeopathic | Type: HUMAN OTC DRUG LABEL
Date: 20241105

ACTIVE INGREDIENTS: THUJA OCCIDENTALIS LEAFY TWIG 6 [hp_X]/10 mL
INACTIVE INGREDIENTS: CEDAR LEAF OIL; TEA TREE OIL; CASTOR OIL

Skin Tag Relief

Drug Facts

Active Ingredients

Thuja Occidentalis 6X (HPUS) 1%

The letters HPUS indicate the component(s) in this product is (are) officially monographed in the Homeopathic Pharmacopeia of the United States.

Purpose

Cutaneous Skin Tags Relief

Uses

Symptomatic treatment of Skin Tags.

Warnings

For external use only.

PREGNANCY OR BREAST FEEDING

If pregnant or breast-feeding, ask a health professional before use.

Avoid using near the eyes or mouth.

KEEP OUT OF REACH OF CHILDREN

Keep out of the reach of children. In case of ingestion call Poison Control Center hotline immediately at 1-800-222-1222.

Do not use if tamper evident seal is broken.

Directions

Apply 3 times daily to affected area. Skin tags will dry and flake away over several week period. Some individuals may be sensitive to essential oil. Skin test for tolerability. If irritation or reaction occurs, discontinue use.

Other ingredients

Cedar Leaf Oil, Melaleuca Alternifollia Leaf Oil (Tea Tree Oil), Ricinus Communis Seed Oil (Castor Oil).

There is no scientific evidence that this product works. The product's claims are based only on theories of homeopathy from the 1700's that are not acceptert by most modern medical experts.